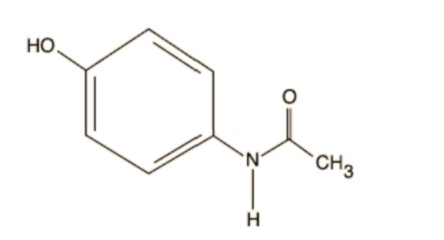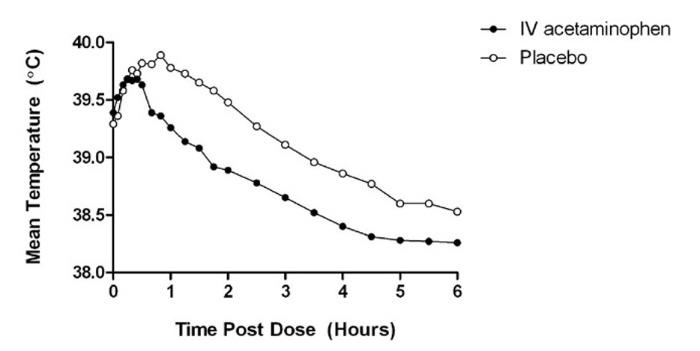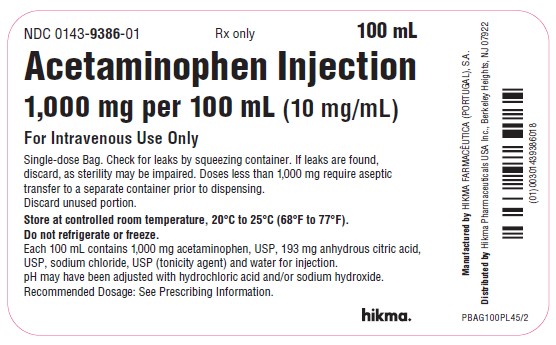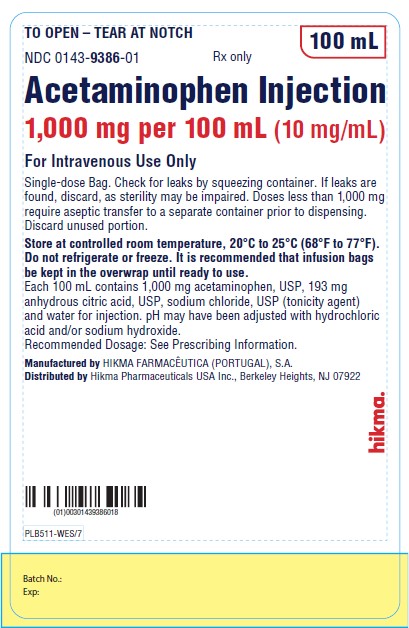 DRUG LABEL: Acetaminophen
NDC: 0143-9386 | Form: INJECTION
Manufacturer: Hikma Pharmaceuticals USA Inc.
Category: prescription | Type: HUMAN PRESCRIPTION DRUG LABEL
Date: 20250818

ACTIVE INGREDIENTS: ACETAMINOPHEN 1000 mg/100 mL
INACTIVE INGREDIENTS: SODIUM CHLORIDE; WATER; HYDROCHLORIC ACID; SODIUM HYDROXIDE; ANHYDROUS CITRIC ACID

HIGHLIGHTS OF PRESCRIBING INFORMATION

These highlights do not include all the information needed to use ACETAMINOPHEN INJECTION safely and effectively. See full prescribing information for ACETAMINOPHEN INJECTION.
ACETAMINOPHEN injection, for intravenous infusion Initial U.S. Approval: 1951

WARNING: RISK OF MEDICATION ERRORS AND HEPATOTOXICITY

See full prescribing information for complete boxed warning.

Take care when prescribing, preparing, and administering Acetaminophen Injection to avoid dosing errors which could result in accidental overdose and death (5.3).

Acetaminophen Injection contains acetaminophen. Acetaminophen has been associated with cases of acute liver failure, at times resulting in liver transplant and death. Most of the cases of liver injury are associated with the use of acetaminophen at doses that exceed the recommended maximum daily limits, and often involve more than one acetaminophen-containing product (5.1).

1 INDICATIONS AND USAGE

Acetaminophen Injection is indicated for the

- Management of mild to moderate pain in adult and pediatric patients 2 years and older. (1)
- Management of moderate to severe pain with adjunctive opioid analgesics in adult and pediatric patients 2 years and older. (1)
- Reduction of fever in adult and pediatric patients. (1)

2 DOSAGE AND ADMINISTRATION

Acetaminophen Injection may be given as a single or repeated dose. (2.1)

Acetaminophen Injection should be administered only as a 15-minute intravenous infusion. (2.5)

Adults and Adolescents Weighing 50 kg and Over:

- 1,000 mg every 6 hours or 650 mg every 4 hours to a maximum of 4,000 mg per day. Minimum dosing interval of 4 hours. (2.2)

Adults and Adolescents Weighing Under 50 kg:

- 15 mg/kg every 6 hours or 12.5 mg/kg every 4 hours to a maximum of 75 mg/kg per day. Minimum dosing interval of 4 hours. (2.2)

Children:

- Children 2 to 12 years of age: 15 mg/kg every 6 hours or 12.5 mg/kg every 4 hours to a maximum of 75 mg/kg per day. Minimum dosing interval of 4 hours. (2.3)

Neonates and Infants:

- Neonates including premature neonates born at greater than or equal to 32 weeks gestational age to 28 days chronological age, 12.5 mg/kg every 6 hours to a maximum of 50 mg/kg per day. Minimum dosing interval of 6 hours. (2.4)

- Infants (29 days to 2 years of age): 15 mg/kg every 6 hours to a maximum of 60 mg/kg per day. Minimum dosing interval of 6 hours. (2.4)

3 DOSAGE FORMS AND STRENGTHS

- Injection: 1,000 mg in 100 mL (10 mg/mL). (3)

4 CONTRAINDICATIONS

Acetaminophen is contraindicated:

- In patients with known hypersensitivity to acetaminophen or to any of the excipients in the IV formulation. (4)
- In patients with severe hepatic impairment or severe active liver disease. (4)

5 WARNINGS AND PRECAUTIONS

- Administration of acetaminophen in doses higher than recommended (by all routes of administration and from all acetaminophen-containing products including combination products) may result in hepatic injury, including the risk of liver failure and death. (5.1)
- Use caution when administering acetaminophen in patients with the following conditions: hepatic impairment or active hepatic disease, in cases of alcoholism, chronic malnutrition, severe hypovolemia, or severe renal impairment (creatinine clearance less than or equal to 30 mL/min). (5.1)
- Discontinue Acetaminophen Injection immediately at the first appearance of skin rash and if symptoms associated with allergy or hypersensitivity occur. Do not use in patients with acetaminophen allergy. (5.2, 5.4)
- Take care when prescribing, preparing, and administering Acetaminophen Injection to avoid dosing errors which could result in accidental overdose and death. (5.3)

6 ADVERSE REACTIONS

The most common adverse reactions in patients treated with Acetaminophen Injection were nausea, vomiting, headache, and insomnia in adult patients; nausea, vomiting, constipation, and pruritus in pediatric patients. (6.1)

To report SUSPECTED ADVERSE REACTIONS, contact Hikma Pharmaceuticals USA Inc. at 1-877-845-0689, or the FDA at 1-800-FDA-1088 or www.fda.gov/medwatch.

7 DRUG INTERACTIONS

- Substances that induce or regulate hepatic cytochrome enzyme CYP2E1 may alter the metabolism of acetaminophen and increase its hepatotoxic potential. (7.1)
- Chronic oral acetaminophen use at a dose of 4,000 mg/day has been shown to cause an increase in international normalized ratio (INR) in some patients who have been stabilized on sodium warfarin as an anticoagulant. (7.2)

8. USE IN SPECIFIC POPULATIONS

- Pediatric Use: The effectiveness of Acetaminophen Injection for the treatment of acute pain in pediatric patients younger than 2 years of age has not been established. The safety and effectiveness of Acetaminophen Injection in pediatric patients is supported by evidence from adequate and well-controlled studies in adults with additional safety and pharmacokinetic data for this age group. (8.4)
- Geriatric Use: No overall differences in safety or effectiveness were observed between geriatric and younger subjects. (8.5)
- Hepatic Impairment: Acetaminophen Injection is contraindicated in patients with severe hepatic impairment or severe active liver disease and should be used with caution in patients with hepatic impairment or active liver disease. (4, 5.1, 8.6)
- Renal Impairment: In cases of severe renal impairment, longer dosing intervals and a reduced total daily dose of acetaminophen may be warranted. (5.1, 8.7)

FULL PRESCRIBING INFORMATION

WARNING: RISK OF MEDICATION ERRORS AND HEPATOTOXICITY

Take care when prescribing, preparing, and administering Acetaminophen Injection to avoid dosing errors which could result in accidental overdose and death [see Warnings and Precautions (5.3)]. In particular, be careful to ensure that:

- the dose in milligrams (mg) and milliliters (mL) is not confused;
- the dosing is based on weight for patients under 50 kg;
- infusion pumps are properly programmed; and
- the total daily dose of acetaminophen from all sources does not exceed maximum daily limits.

Acetaminophen Injection contains acetaminophen. Acetaminophen has been associated with cases of acute liver failure, at times resulting in liver transplant and death. Most of the cases of liver injury are associated with the use of acetaminophen at doses that exceed the recommended maximum daily limits, and often involve more than one acetaminophen-containing product [see Warnings and Precautions (5.1)].

1 INDICATIONS AND USAGE

Acetaminophen Injection is indicated for

- the management of mild to moderate pain in adult and pediatric patients 2 years and older.
- the management of moderate to severe pain with adjunctive opioid analgesics in adult and pediatric patients 2 years and older.
- the reduction of fever in adult and pediatric patients.

2 DOSAGE AND ADMINISTRATION

2.1 Important Dosage and Administration Instructions

Acetaminophen Injection may be given as a single or repeated dose for the treatment of acute pain or fever. No dose adjustment is required when converting between oral acetaminophen and Acetaminophen Injection dosing in adults and adolescents who weigh 50 kg and above. Calculated maximum daily dose of acetaminophen is based on all routes of administration (i.e., intravenous, oral, and rectal) and all products containing acetaminophen. Exceeding the maximum mg/kg daily dose of acetaminophen as described in Tables 1-3 may result in hepatic injury, including the risk of liver failure and death. To avoid the risk of overdose, ensure that the total amount of acetaminophen from all routes and from all sources does not exceed the maximum recommended dose.

2.2 Recommended Dosage: Adults and Adolescents

Adults and adolescents weighing 50 kg and over: the recommended dosage of Acetaminophen Injection is 1,000 mg every 6 hours or 650 mg every 4 hours, with a maximum single dose of Acetaminophen Injection of 1,000 mg, a minimum dosing interval of 4 hours, and a maximum daily dose of acetaminophen of 4,000 mg per day (includes all routes of administration and all acetaminophen-containing products including combination products).

Adults and adolescents weighing under 50 kg: the recommended dosage of Acetaminophen Injection is 15 mg/kg every 6 hours or 12.5 mg/kg every 4 hours, with a maximum single dose of Acetaminophen Injection of 15 mg/kg, a minimum dosing interval of 4 hours, and a maximum daily dose of acetaminophen of 75 mg/kg per day (includes all routes of administration and all acetaminophen-containing products including combination products).

Table 1. Dosing for Adults and Adolescents

Age group | Dose given every 4 hours | Dose given every 6 hours | Maximum single dose | Maximum total daily dose of acetaminophen (by all routes)
Adults and adolescents (13 years and older) weighing greater than or equal to 50 kg | 650 mg | 1,000 mg | 1,000 mg | 4,000 mg in 24 hours
Adults and adolescents (13 years and older) weighing less than 50 kg | 12.5 mg/kg | 15 mg/kg | 15 mg/kg (up to 750 mg) | 75 mg/kg in 24 hours (up to 3,750 mg)

2.3 Recommended Dosage: Children

Children 2 to 12 years of age: the recommended dosage of Acetaminophen Injection is 15 mg/kg every 6 hours or 12.5 mg/kg every 4 hours, with a maximum single dose of Acetaminophen Injection of 15 mg/kg, a minimum dosing interval of 4 hours, and a maximum daily dose of acetaminophen of 75 mg/kg per day.

Table 2. Dosing for Children

Age group | Dose given every 4 hours | Dose given every 6 hours | Maximum single dose | Maximum total daily dose of acetaminophen (by all routes)
Children 2 to 12 years of age | 12.5 mg/kg | 15 mg/kg | 15 mg/kg (up to 750 mg) | 75 mg/kg in 24 hours (up to 3,750 mg)

2.4 Recommended Dosage for Treatment of Fever in Neonates and Infants

Neonates, including premature neonates born at greater than or equal to 32 weeks gestational age, up to 28 days chronological age: the recommended dosage of Acetaminophen Injection is 12.5 mg/kg every 6 hours, to a maximum daily dose of acetaminophen of 50 mg/kg per day, with a minimum dosing interval of 6 hours.

Infants 29 days to 2 years of age: the recommended dosage of Acetaminophen Injection is 15 mg/kg every 6 hours, to a maximum daily dose of acetaminophen of 60 mg/kg per day, with a minimum dosing interval of 6 hours.

Table 3. Dosing for Treatment of Fever in Neonates and Infants

Age group | Dose given every 6 hours | Maximum total daily dose of acetaminophen (by all routes)
Neonates (birth to 28 days) | 12.5 mg/kg | 50 mg/kg
Infants (29 days to 2 years) | 15 mg/kg | 60 mg/kg

2.5 Instructions for Intravenous Administration

For adult and adolescent patients weighing greater than or equal to 50 kg requiring 1,000 mg doses of Acetaminophen Injection, administer by intravenous infusion. Acetaminophen Injection may be administered without further dilution. Examine the bag contents before dose preparation or administering. DO NOT USE if particulate matter or discoloration is observed. Check for minute leaks by firmly squeezing the bag. If leaks are detected, discard the solution, as sterility may be impaired. Keep the infusion bags in the overwrap until ready to use. Administer the contents of the bag intravenously over 15 minutes. Use aseptic technique when preparing Acetaminophen Injection for intravenous infusion. Do not add other medications to the Acetaminophen Injection bag or infusion device.

For doses less than 1,000 mg, the appropriate dose must be withdrawn from the bag and placed into a separate container prior to administration. Using aseptic technique, withdraw the appropriate dose (650 mg or weight-based) from an intact Acetaminophen Injection bag and place the measured dose in a separate empty, sterile container (e.g., glass bottle, plastic intravenous container, or syringe) for intravenous infusion to avoid the inadvertent delivery and administration of the total volume of the commercially available container. The entire 100 mL bag of Acetaminophen Injection is not intended for use in patients weighing less than 50 kg. Acetaminophen Injection is a single-dose bag and the unused portion must be discarded.

Place small volume pediatric doses up to 60 mL in volume in a syringe and administer over 15 minutes using a syringe pump.

Monitor the end of the infusion in order to prevent the possibility of an air embolism, especially in cases where the Acetaminophen Injection infusion is the primary infusion.

After opening the overwrap, immediate use of Acetaminophen Injection is recommended. However the stability of the product after it has been removed from the overwrap has been demonstrated for 24 hours.

Do not add other medications to the Acetaminophen Injection solution. Diazepam and chlorpromazine hydrochloride are physically incompatible with Acetaminophen Injection, therefore do not administer simultaneously.

3 DOSAGE FORMS AND STRENGTHS

Injection: Acetaminophen Injection is a sterile, clear, colorless to faint yellow, non-pyrogenic, preservative free, isotonic formulation containing 1,000 mg of acetaminophen in 100 mL (10 mg/mL) in single-dose bags.

4 CONTRAINDICATIONS

Acetaminophen is contraindicated:

- in patients with known hypersensitivity to acetaminophen or to any of the excipients in the intravenous formulation.
- in patients with severe hepatic impairment or severe active liver disease [see Warnings and Precautions (5.1)].

5 WARNINGS AND PRECAUTIONS

5.1 Hepatic Injury

Administration of acetaminophen in doses higher than recommended may result in hepatic injury, including the risk of liver failure and death [see Overdosage (10)]. Do not exceed the maximum recommended daily dose of acetaminophen [see Dosage and Administration (2)]. The maximum recommended daily dose of acetaminophen includes all routes of acetaminophen administration and all acetaminophen-containing products administered, including combination products.

Use caution when administering acetaminophen in patients with the following conditions: hepatic impairment or active hepatic disease, alcoholism, chronic malnutrition, severe hypovolemia (e.g., due to dehydration or blood loss), or severe renal impairment (creatinine clearance less than or equal to 30 mL/min) [see Use in Specific Populations (8.6, 8.7)].

5.2 Serious Skin Reactions

Rarely, acetaminophen may cause serious skin reactions such as acute generalized exanthematous pustulosis (AGEP), Stevens-Johnson Syndrome (SJS), and toxic epidermal necrolysis (TEN), which can be fatal. Patients should be informed about the signs of serious skin reactions, and use of the drug should be discontinued at the first appearance of skin rash or any other sign of hypersensitivity.

5.3 Risk of Medication Errors

Take care when prescribing, preparing, and administering Acetaminophen Injection in order to avoid dosing errors which could result in accidental overdose and death. In particular, be careful to ensure that:

- the dose in milligrams (mg) and milliliters (mL) is not confused;
- the dosing is based on weight for patients under 50 kg;
- infusion pumps are properly programmed; and
- the total daily dose of acetaminophen from all sources does not exceed maximum daily limits [see Dosage and Administration (2)].

5.4 Allergy and Hypersensitivity

There have been post-marketing reports of hypersensitivity and anaphylaxis associated with the use of acetaminophen. Clinical signs included swelling of the face, mouth, and throat, respiratory distress, urticaria, rash, and pruritus. There were infrequent reports of life-threatening anaphylaxis requiring emergent medical attention. Discontinue Acetaminophen Injection immediately if symptoms associated with allergy or hypersensitivity occur. Do not use Acetaminophen Injection in patients with acetaminophen allergy.

6 ADVERSE REACTIONS

The following serious adverse reactions are discussed elsewhere in the labeling:

- Hepatic Injury [see Warnings and Precautions (5.1)]
- Serious Skin Reactions [see Warnings and Precautions (5.2)]
- Allergy and Hypersensitivity [see Warnings and Precautions (5.4)]

6.1 Clinical Trials Experience

Because clinical trials are conducted under widely varying conditions, adverse reaction rates observed cannot be directly compared to rates in other clinical trials and may not reflect the rates observed in practice.

Adult Population

A total of 1,020 adult patients have received Acetaminophen Injection in clinical trials, including 37.3% (n=380) who received 5 or more doses, and 17.0% (n=173) who received more than 10 doses. Most patients were treated with Acetaminophen Injection 1,000 mg every 6 hours. A total of 13.1% (n=134) received Acetaminophen Injection 650 mg every 4 hours.

All adverse reactions that occurred in adult patients treated with either Acetaminophen Injection or placebo in repeated dose, placebo-controlled clinical trials at an incidence greater than or equal to 3% and at a greater frequency than placebo are listed in Table 4. The most common adverse events in adult patients treated with Acetaminophen Injection (incidence greater than or equal to 5% and greater than placebo) were nausea, vomiting, headache, and insomnia.

Table 4. Treatment-Emergent Adverse Reactions Occurring in Greater than or Equal to 3% of Acetaminophen Injection-treated Adult Patients and at a Greater Frequency than Placebo in Placebo-Controlled, Repeated Dose Studies

System Organ Class – Preferred Term | Acetaminophen Injection (N=402) n (%) | Placebo (N=379) n (%)
Gastrointestinal Disorders; Nausea; Vomiting | 138 (34); 62 (15) | 119 (31); 42 (11)
General Disorders and Administration Site Conditions; Pyrexia* | 22 (5) | 52 (14)
Nervous System Disorders; Headache | 39 (10) | 33 (9)
Psychiatric Disorders; Insomnia | 30 (7) | 21 (5)

* Pyrexia adverse reaction frequency data is included in order to alert healthcare practitioners that the antipyretic effects of Acetaminophen Injection may mask fever.

Other Adverse Reactions Observed During Clinical Studies of Acetaminophen Injection in Adults The following additional treatment-emergent adverse reactions were reported by adult subjects treated with Acetaminophen Injection in all clinical trials (n=1,020) that occurred with an incidence of at least 1% and at a frequency greater than placebo (n=525).

Blood and lymphatic system disorders: anemia

General disorders and administration site conditions: fatigue, infusion site pain, edema peripheral

Investigations: aspartate aminotransferase increased, breath sounds abnormal

Metabolism and nutrition disorders: hypokalemia

Musculoskeletal and connective tissue disorders: muscle spasms, trismus

Psychiatric disorders: anxiety

Respiratory, thoracic and mediastinal disorders: dyspnea

Vascular disorders: hypertension, hypotension

Pediatric Population

A total of 483 pediatric patients (72 neonates, 167 infants, 171 children, and 73 adolescents) have received Acetaminophen Injection in active-controlled (n=250) and open-label clinical trials (n=225), including 43.9% (n=212) who received 5 or more doses and 31.2% (n=153) who received more than 10 doses.

Pediatric patients received Acetaminophen Injection doses up to 15 mg/kg on an every 4 hours, every 6 hours, or every 8 hours schedule. The maximum exposure was 7.7, 6.4, 6.8, and 7.1 days in neonates, infants, children, and adolescents, respectively.

The most common adverse events (incidence greater than or equal to 5%) in pediatric patients treated with Acetaminophen Injection were nausea, vomiting, constipation, and pruritus.

Other Adverse Reactions Observed During Clinical Studies of Acetaminophen Injection in Pediatrics

The following additional treatment-emergent adverse reactions were reported by pediatric subjects treated with Acetaminophen Injection (n=483) that occurred with an incidence of at least 1%.

Blood and lymphatic system disorders: anemia

Gastrointestinal disorders: diarrhea

General disorders and administration site conditions: pyrexia, injection site pain Metabolism and nutrition disorders: hypokalemia, hypomagnesemia, hypoalbuminemia, hypophosphatemia

Musculoskeletal and connective tissue disorders: muscle spasm

Nervous system disorders: headache Psychiatric disorders: agitation Renal and urinary disorders: oliguria

Respiratory, thoracic, and mediastinal disorders: atelectasis, pleural effusion, pulmonary edema, stridor, wheezing

Vascular disorders: hypotension, hypertension

7 DRUG INTERACTIONS

7.1 Effects of Other Substances on Acetaminophen

Substances that induce or regulate hepatic cytochrome enzyme CYP2E1 may alter the metabolism of acetaminophen and increase its hepatotoxic potential. The clinical consequences of these effects have not been established. Effects of ethanol are complex, because excessive alcohol usage can induce hepatic cytochromes, but ethanol also acts as a competitive inhibitor of the metabolism of acetaminophen.

7.2 Anticoagulants

Chronic oral acetaminophen use at a dose of 4,000 mg/day has been shown to cause an increase in international normalized ratio (INR) in some patients who have been stabilized on sodium warfarin as an anticoagulant. As no studies have been performed evaluating the short-term use of Acetaminophen Injection in patients on oral anticoagulants, more frequent assessment of INR may be appropriate in such circumstances.

8. USE IN SPECIFIC POPULATIONS

8.1 Pregnancy

Risk Summary

Published epidemiological studies with oral acetaminophen use during pregnancy have not reported a clear association with acetaminophen use and birth defects, miscarriage, or adverse maternal or fetal outcomes [see Data]. Animal reproduction studies have not been conducted with IV acetaminophen. Reproductive and developmental studies in rats and mice from the published literature identified adverse events at clinically relevant doses with acetaminophen. Treatment of pregnant rats with doses of acetaminophen approximately equal to the maximum human daily dose (MHDD) showed evidence of fetotoxicity and increases in bone variations in the fetuses. In another study, necrosis was observed in the liver and kidney of both pregnant rats and fetuses at doses approximately equal to the MHDD. In mice and rats treated with acetaminophen at doses within the clinical dosing range, cumulative adverse effects on reproductive capacity were reported. In mice, a reduction in number of litters of the parental mating pair was observed as well as retarded growth, abnormal sperm in their offspring and reduced birth weight in the next generation. In rats, female fertility was decreased following in utero exposure to acetaminophen [see Data].

The estimated background risk of major birth defects and miscarriages for the indicated population is unknown. All pregnancies have a background risk of birth defect, loss, or other adverse outcomes. In the

U.S. general population, the estimated background risk of major birth defects and miscarriage in clinically recognized pregnancies is 2-4% and 15-20%, respectively.

Data

Human Data

The results from a large population-based prospective cohort, including data from 26,424 women with live born singletons who were exposed to oral acetaminophen during the first trimester, indicate no increased risk for congenital malformations, compared to a control group of unexposed children. The rate of congenital malformations (4.3%) was similar to the rate in the general population. A population-based, case-control study from the National Birth Defects Prevention Study showed that 11,610 children with prenatal exposure to acetaminophen during the first trimester had no increased risk of major birth defects compared to 4,500 children in the control group. Other epidemiological data showed similar results.

However, these studies cannot definitely establish the absence of any risk because of methodological limitations, including recall bias.

Animal Data

Studies in pregnant rats that received oral acetaminophen during organogenesis at doses up to 0.85 times the maximum human daily dose (MHDD = 4 grams/day, based on a body surface area comparison) showed evidence of fetotoxicity (reduced fetal weight and length) and a dose-related increase in bone variations (reduced ossification and rudimentary rib changes). Offspring had no evidence of external, visceral, or skeletal malformations. When pregnant rats received oral acetaminophen throughout gestation at doses of 1.2 times the MHDD (based on a body surface area comparison), areas of necrosis occurred in both the liver and kidney of pregnant rats and fetuses. These effects did not occur in animals that received oral acetaminophen at doses 0.3 times the MHDD, based on a body surface area comparison.

In a continuous breeding study, pregnant mice received 0.25, 0.5, or 1.0% acetaminophen via the diet (357, 715, or 1,430 mg/kg/day). These doses are approximately 0.43, 0.87, and 1.7 times the MHDD, respectively, based on a body surface area comparison. A dose related reduction in body weights of fourth and fifth litter offspring of the treated mating pair occurred during lactation and post-weaning at all doses. Animals in the high dose group had a reduced number of litters per mating pair, male offspring with an increased percentage of abnormal sperm, and reduced birth weights in the next generation pups.

8.2 Lactation

Risk Summary

There is no information regarding the presence of acetaminophen in human milk, the effects on the breastfed infant, or the effects on milk production. However, limited published studies report that acetaminophen passes rapidly into human milk with similar levels in the milk and plasma. Average and maximum neonatal doses of 1% and 2%, respectively, of the weight-adjusted maternal dose are reported after a single oral administration of 1 gram APAP. There is one well-documented report of a rash in a breastfed infant that resolved when the mother stopped acetaminophen use and recurred when she resumed acetaminophen use. The developmental and health benefits of breastfeeding should be considered along with the mother’s clinical need for Acetaminophen Injection and any potential adverse effects on the breastfed infant from Acetaminophen Injection or from the underlying maternal condition

8.3 Females and Males of Reproductive Potential

Based on animal data use of acetaminophen may cause reduced fertility in males and females of reproductive potential. It is not known whether these effects on fertility are reversible. Published animal studies reported that oral acetaminophen treatment of male animals at doses that are 1.2 times the MHDD and greater (based on a body surface area comparison) result in decreased testicular weights, reduced spermatogenesis, and reduced fertility. In female animals given the same doses, reduced implantation sites were reported. Additional published animal studies indicate that acetaminophen exposure in utero adversely impacts reproductive capacity of both male and female offspring at clinically relevant exposures [see Nonclinical Toxicology (13.1)].

8.4 Pediatric Use

Treatment of Acute Pain

The safety and effectiveness of Acetaminophen Injection for the treatment of acute pain in pediatric patients ages 2 years and older is supported by evidence from adequate and well-controlled studies of Acetaminophen Injection in adults and safety and pharmacokinetic data from adult and 483 pediatric patients across all age groups [see Dosage and Administration (2.3) and Clinical Pharmacology (12.3)].

The effectiveness of Acetaminophen Injection for the treatment of acute pain in pediatric patients younger than 2 years of age has not been established.

In patients younger than 2 years, efficacy was not demonstrated in a double-blind, placebo-controlled study of 198 pediatric patients younger than 2 years. Pediatric patients less than 2 years of age, including neonates from 28 to 40 weeks gestational age at birth, were randomized to receive opioid plus acetaminophen or opioid plus placebo. No difference in analgesic effect of intravenous acetaminophen, measured by assessment of reduced need for additional opioid treatment for pain control, was observed.

Treatment of Fever

The safety and effectiveness of Acetaminophen Injection for the treatment of fever in pediatric patients, including premature neonates born at greater than or equal to 32 weeks gestational age is supported by adequate and well-controlled studies of Acetaminophen Injection in adults, clinical studies in 244 pediatric patients 2 years and older, and safety and pharmacokinetic data from 239 patients younger than 2 years including neonates greater than or equal to 32 weeks gestational age.

8.5 Geriatric Use

Of the total number of subjects in clinical studies of Acetaminophen Injection, 15% were age 65 and over, while 5% were age 75 and over. No overall differences in safety or effectiveness were observed between these subjects and younger subjects, and other reported clinical experience has not identified differences in responses between the elderly and younger patients, but greater sensitivity of some older individuals cannot be ruled out.

8.6 Patients with Hepatic Impairment

Acetaminophen is contraindicated in patients with severe hepatic impairment or severe active liver disease and should be used with caution in patients with hepatic impairment or active liver disease [see Warnings and Precautions (5.1) and Clinical Pharmacology (12)]. A reduced total daily dose of acetaminophen may be warranted.

8.7 Patients with Renal Impairment

In cases of severe renal impairment (creatinine clearance less than or equal to 30 mL/min), longer dosing intervals and a reduced total daily dose of acetaminophen may be warranted.

10 OVERDOSAGE

Signs and Symptoms

In acute acetaminophen overdosage, dose-dependent, potentially fatal hepatic necrosis is the most serious adverse effect. Renal tubular necrosis, hypoglycemic coma, and thrombocytopenia may also occur.

Plasma acetaminophen levels greater than 300 mcg/mL at 4 hours after oral ingestion were associated with hepatic damage in 90% of patients; minimal hepatic damage is anticipated if plasma levels at 4 hours are less than 150 mcg/mL or less than 37.5 mcg/mL at 12 hours after ingestion. Early symptoms following a potentially hepatotoxic overdose may include: nausea, vomiting, diaphoresis, and general malaise.

Clinical and laboratory evidence of hepatic toxicity may not be apparent until 48 to 72 hours post-ingestion.

Treatment

If an acetaminophen overdose is suspected, obtain a serum acetaminophen assay as soon as possible, but no sooner than 4 hours following oral ingestion. Obtain liver function studies initially and repeat at 24-hour intervals. Administer the antidote N-acetylcysteine (NAC) as early as possible. As a guide to treatment of acute ingestion, the acetaminophen level can be plotted against time since oral ingestion on a nomogram (Rumack-Matthew). The lower toxic line on the nomogram is equivalent to 150 mcg/mL at 4 hours and 37.5 mcg/mL at 12 hours. If serum level is above the lower line, administer the entire course of NAC treatment. Withhold NAC therapy if the acetaminophen level is below the lower line.

For additional information, call a poison control center at 1-800-222-1222.

11 DESCRIPTION

Acetaminophen is a non-salicylate antipyretic and non-opioid analgesic agent. Its chemical name is N-acetyl-p-aminophenol. Acetaminophen has a molecular weight of 151.16. Its structural formula is:

Acetaminophen Injection is a sterile, clear, colorless to faint yellow, non-pyrogenic, isotonic formulation of acetaminophen intended for intravenous infusion. It has a pH of approximately 5.5 and an osmolality of approximately 290 mOsm/kg. Each 100 mL contains 1,000 mg acetaminophen, USP, 193 mg anhydrous citric acid, USP, sodium chloride, USP (tonicity agent) and water for injection, USP. pH is adjusted with hydrochloric acid and/or sodium hydroxide.

12 CLINICAL PHARMACOLOGY

12.1 Mechanism of Action

The precise mechanism of the analgesic and antipyretic properties of acetaminophen is not established but is thought to primarily involve central actions.

12.2 Pharmacodynamics

Acetaminophen has been shown to have analgesic and antipyretic activities in animal and human studies.

Single doses of Acetaminophen Injection up to 3,000 mg and repeated doses of 1,000 mg every 6 hours for 48 hours have not been shown to cause a significant effect on platelet aggregation. Acetaminophen does not have any immediate or delayed effects on small-vessel hemostasis. Clinical studies of both healthy subjects and patients with hemophilia showed no significant changes in bleeding time after receiving multiple doses of oral acetaminophen.

12.3 Pharmacokinetics

Distribution

The pharmacokinetics of Acetaminophen Injection have been studied in patients and healthy subjects up to 60 years old. The pharmacokinetic profile of Acetaminophen Injection has been demonstrated to be dose proportional in adults following administration of single doses of 500, 650, and 1,000 mg.

The maximum concentration (Cmax) occurs at the end of the 15-minute intravenous infusion of Acetaminophen Injection. Compared to the same dose of oral acetaminophen, the Cmax following administration of Acetaminophen Injection is up to 70% higher, while overall exposure (area under the concentration time curve [AUC]) is very similar.

Pharmacokinetic parameters of Acetaminophen Injection (AUC, Cmax, terminal elimination half-life [T½], systemic clearance [CL], and volume of distribution at steady state [Vss]) following administration of a single intravenous dose of 15 mg/kg in children and adolescents and 1,000 mg in adults are summarized in Table 5.

Table 5. Acetaminophen Injection Pharmacokinetic Parameters

Subpopulations | Mean (SD)
Subpopulations | AUC 0-6h; (µg × h/mL) | Cmax (µg/mL) | T½ (h) | CL; (L/h/kg) | Vss (L/kg)
Children | 38 (8) | 29 (7) | 3.0 (1.5) | 0.34 (0.10) | 1.2 (0.3)
Adolescents | 41 (7) | 31 (9) | 2.9 (0.7) | 0.29 (0.08) | 1.1 (0.3)
Adults | 43 (11) | 28 (21) | 2.4 (0.6) | 0.27 (0.08) | 0.8 (0.2)

The concentrations of acetaminophen observed in neonates greater than 32 weeks gestational age at birth treated with 12.5 mg/kg dose are similar to infants, children and adolescents treated with a 15 mg/kg dose, and similar to adults treated with a 1,000 mg dose.

At therapeutic levels, binding of acetaminophen to plasma proteins is low (ranging from 10% to 25%). Acetaminophen appears to be widely distributed throughout most body tissues except fat.

Elimination

Acetaminophen is primarily metabolized in the liver and its metabolites are mainly excreted in the urine.

Metabolism

Acetaminophen is primarily metabolized in the liver by first-order kinetics and involves three principal separate pathways: Conjugation with glucuronide, conjugation with sulfate, and oxidation via the cytochrome P450 enzyme pathway, primarily CYP2E1, to form a reactive intermediate metabolite

(N-acetyl-p-benzoquinone imine or NAPQI). With therapeutic doses, NAPQI undergoes rapid conjugation with glutathione and is then further metabolized to form cysteine and mercapturic acid conjugates.

Excretion

Acetaminophen metabolites are mainly excreted in the urine. Less than 5% is excreted in the urine as unconjugated (free) acetaminophen and more than 90% of the administered dose is excreted within 24 hours.

13 NONCLINICAL TOXICOLOGY

13.1 Carcinogenesis, Mutagenesis, Impairment of Fertility

Carcinogenesis

Long-term studies in mice and rats have been completed by the National Toxicology Program to evaluate the carcinogenic potential of acetaminophen. In 2-year feeding studies, F344/N rats and B6C3F1 mice were fed a diet containing acetaminophen up to 6,000 ppm. Female rats demonstrated equivocal evidence of carcinogenic activity based on increased incidences of mononuclear cell leukemia at 0.8 times the maximum human daily dose (MHDD) of 4 grams/day, based on a body surface area comparison. In contrast, there was no evidence of carcinogenic activity in male rats (0.7 times) or mice (1.2-1.4 times the MHDD, based on a body surface area comparison).

Mutagenesis

Acetaminophen was not mutagenic in the bacterial reverse mutation assay (Ames test). In contrast, acetaminophen tested positive in the in vitro mouse lymphoma assay and the in vitro chromosomal aberration assay using human lymphocytes. In the published literature, acetaminophen has been reported to be clastogenic when administered a dose of 1,500 mg/kg/day to the rat model (3.6-times the MHDD, based on a body surface area comparison). In contrast, no clastogenicity was noted at a dose of 750 mg/kg/day (1.8-times the MHDD, based on a body surface area comparison), suggesting a threshold effect.

Impairment of Fertility

In studies conducted by the National Toxicology Program, fertility assessments have been completed in Swiss mice via a continuous breeding study. There were no effects on fertility parameters in mice consuming up to 1.7 times the MHDD of acetaminophen, based on a body surface area comparison.

Although there was no effect on sperm motility or sperm density in the epididymis, there was a significant increase in the percentage of abnormal sperm in mice consuming 1.7 times the MHDD (based on a body surface area comparison) and there was a reduction in the number of mating pairs producing a fifth litter at this dose, suggesting the potential for cumulative toxicity with chronic administration of acetaminophen near the upper limit of daily dosing.

Published studies in rodents report that oral acetaminophen treatment of male animals at doses that are 1.2 times the MHDD and greater (based on a body surface area comparison) result in decreased testicular weights, reduced spermatogenesis, reduced fertility, and reduced implantation sites in females given the same doses. These effects appear to increase with the duration of treatment.

In a published mouse study, oral administration of 50 mg/kg acetaminophen to pregnant mice from Gestation Day 7 to delivery (0.06 times the MHDD, based on a body surface area comparison) reduced the number of primordial follicles in female offspring and reduced the percentage of full term pregnancies and number of pups born to these females exposed to acetaminophen in utero.

In a published study, oral administration of 350 mg/kg acetaminophen to pregnant rats (0.85 times the MHDD, based on a body surface area comparison) from Gestation Day 13 to 21 (dams) reduced the number of germ cells in the fetal ovary, decreased ovary weight, and reduced the number of pups per litter in F1 females as well as reduced ovary weights in F2 females.

14 CLINICAL STUDIES

14.1 Adult Acute Pain

The efficacy of Acetaminophen Injection in the treatment of acute pain in adults was evaluated in two randomized, double-blind, placebo-controlled clinical trials in patients with postoperative pain.

Pain Study 1 evaluated the analgesic efficacy of repeated doses of Acetaminophen Injection 1,000 mg vs. placebo every 6 hours for 24 hours in 101 patients with moderate to severe pain following total hip or knee replacement. Acetaminophen Injection was statistically superior to placebo for reduction in pain intensity over 24 hours. There was an attendant decrease in opioid consumption, the clinical benefit of which was not demonstrated.

Pain Study 2 evaluated the analgesic efficacy of repeated doses of Acetaminophen Injection 1,000 mg every 6 hours or 650 mg every 4 hours for 24 hours versus placebo in the treatment of 244 patients with moderate to severe postoperative pain after abdominal laparoscopic surgery. Patients receiving Acetaminophen Injection experienced a statistically significant greater reduction in pain intensity over 24 hours compared to placebo.

14.2 Adult Fever

The efficacy of Acetaminophen Injection 1,000 mg in the treatment of adult fever was evaluated in one randomized, double-blind, placebo-controlled clinical trial. The study was a 6-hour, single-dose, endotoxin-induced fever study in 60 healthy adult males. A statistically significant antipyretic effect of Acetaminophen Injection was demonstrated through 6 hours in comparison to placebo. The mean temperature over time is shown in Figure 1.

Figure 1: Mean Temperature (°C) Over Time

14.3 Pediatric Acute Pain and Fever

Acetaminophen Injection was studied in pediatric patients in three active-controlled trials and three open-label safety and pharmacokinetic trials [see Use in Specific Populations (8.4)].

16 HOW SUPPLIED/STORAGE AND HANDLING

Acetaminophen Injection is supplied in a single-dose, ready-to-use flexible plastic infusion bag in a foil laminate overwrap containing 1,000 mg acetaminophen per 100 mL (10 mg/mL). The infusion bags and ports are manufactured with materials that do not contain latex. Carton of 10 bags, NDC 0143-9386-10.

Acetaminophen Injection is a sterile, clear, colorless to faint yellow, non-pyrogenic, isotonic formulation of acetaminophen intended for intravenous infusion.

Acetaminophen Injection should be stored at 20°C to 25°C (68°F to 77°F) [see USP Controlled Room Temperature]. For single-dose only. It is recommended that infusion bags be kept in the overwrap until ready to use. Once removed from the overwrap, unused Acetaminophen Injection has stability for 24 hours. The product must be used within 4 hours after the bags are pierced. However, immediate use of the pierced bags is recommended. Do not refrigerate or freeze.

Manufactured by:

HIKMA FARMACÊUTICA (PORTUGAL), S.A.

Estrada do Rio da Mó, 8, 8A e 8B – Fervença – 2705-906 Terrugem SNT, PORTUGAL

Distributed by:

Hikma Pharmaceuticals USA Inc.

Berkeley Heights, NJ 07922

PIN571-WES/4

Revised: 4/2024

PRINCIPAL DISPLAY PANEL

NDC 0143-9386-01 Rx only 100 mL

Acetaminophen Injection

1,000 mg per 100 mL (10 mg/mL)

For Intravenous Use Only

PRINCIPAL DISPLAY PANEL - OVERWRAP

TO OPEN - TEAR AT NOTCH

NDC 0143-9386-01 Rx only 100 mL

Acetaminophen Injection

1,000 mg per 100 mL (10 mg/mL)

For Intravenous Use Only